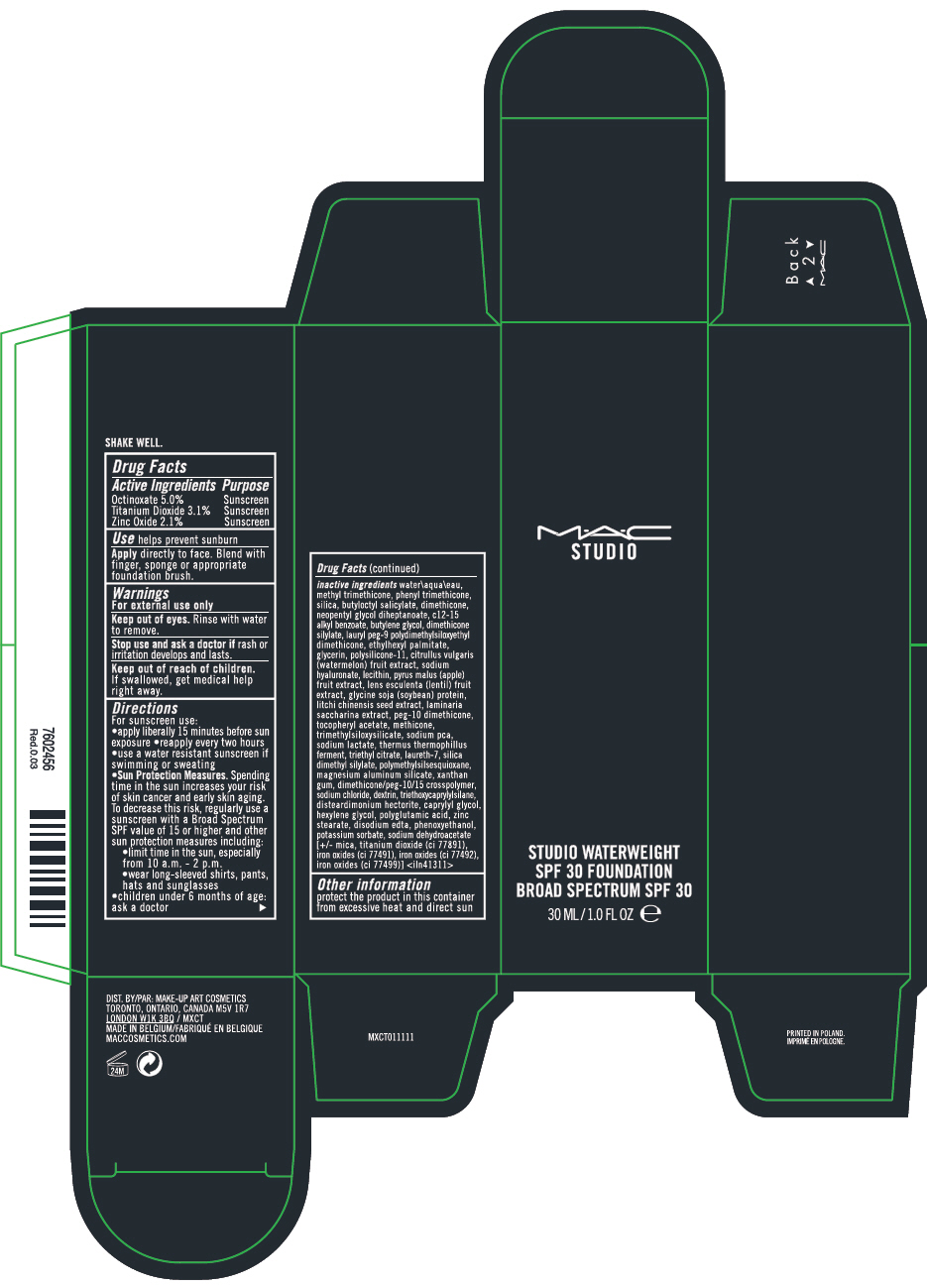 DRUG LABEL: MAC STUDIO WATERWEIGHT SPF 30 BROAD SPECTRUM FOUNDATION
NDC: 40046-0075 | Form: LIQUID
Manufacturer: MAKEUP ART COSMETICS
Category: otc | Type: HUMAN OTC DRUG LABEL
Date: 20241217

ACTIVE INGREDIENTS: OCTINOXATE 0.05425 g/100 mL; TITANIUM DIOXIDE 0.03364 g/100 mL; ZINC OXIDE 0.02279 g/100 mL
INACTIVE INGREDIENTS: WATER; METHYL TRIMETHICONE; PHENYL TRIMETHICONE; SILICON DIOXIDE; BUTYLOCTYL SALICYLATE; DIMETHICONE; NEOPENTYL GLYCOL DIHEPTANOATE; ALKYL (C12-15) BENZOATE; BUTYLENE GLYCOL; LAURYL PEG-9 POLYDIMETHYLSILOXYETHYL DIMETHICONE; ETHYLHEXYL PALMITATE; GLYCERIN; DIMETHICONE/VINYL DIMETHICONE CROSSPOLYMER (SOFT PARTICLE); WATERMELON; HYALURONATE SODIUM; APPLE; LENS CULINARIS FRUIT; SOYBEAN; LITCHI CHINENSIS SEED; SACCHARINA LATISSIMA; .ALPHA.-TOCOPHEROL ACETATE; SODIUM PYRROLIDONE CARBOXYLATE; SODIUM LACTATE; THERMUS THERMOPHILUS LYSATE; TRIETHYL CITRATE; LAURETH-7; SILICA DIMETHYL SILYLATE; MAGNESIUM ALUMINUM SILICATE; XANTHAN GUM; SODIUM CHLORIDE; ICODEXTRIN; TRIETHOXYCAPRYLYLSILANE; DISTEARDIMONIUM HECTORITE; CAPRYLYL GLYCOL; HEXYLENE GLYCOL; ZINC STEARATE; EDETATE DISODIUM; PHENOXYETHANOL; POTASSIUM SORBATE; SODIUM DEHYDROACETATE; MICA; FERRIC OXIDE RED; FERRIC OXIDE YELLOW; FERROSOFERRIC OXIDE

MAC STUDIO WATERWEIGHT SPF 30 BROAD SPECTRUM FOUNDATION
SUNSCREEN

Drug Facts

ACTIVE INGREDIENT

Active Ingredients | Purpose
Octinoxate 5.0% | Sunscreen
Titanium Dioxide 3.1% | Sunscreen
Zinc Oxide 2.1% | Sunscreen

Use

helps prevent sunburn

Apply directly to face. Blend with finger, sponge or appropriate foundation brush.

Warnings

For external use only

WHEN USING

Keep out of eyes. Rinse with water to remove.

Stop use and ask a doctor if rash or irritation develops and lasts.

Keep out of reach of children. If swallowed, get medical help right away.

Directions

For sunscreen use:

- apply liberally 15 minutes before sun exposure
- reapply every two hours
- use a water resistant sunscreen if swimming or sweating
- Sun Protection Measures. Spending time in the sun increases your risk of skin cancer and early skin aging. To decrease this risk, regularly use a sunscreen with a Broad Spectrum SPF value of 15 or higher and other sun protection measures including:
  - limit time in the sun, especially from 10 a.m. - 2 p.m.
  - wear long-sleeved shirts, pants, hats and sunglasses
- children under 6 months of age: ask a doctor

inactive ingredients

water\aqua\eau, methyl trimethicone, phenyl trimethicone, silica, butyloctyl salicylate, dimethicone, neopentyl glycol diheptanoate, c12-15 alkyl benzoate, butylene glycol, dimethicone silylate, lauryl peg-9 polydimethylsiloxyethyl dimethicone, ethylhexyl palmitate, glycerin, polysilicone-11, citrullus vulgaris (watermelon) fruit extract, sodium hyaluronate, lecithin, pyrus malus (apple) fruit extract, lens esculenta (lentil) fruit extract, glycine soja (soybean) protein, litchi chinensis seed extract, laminaria saccharina extract, peg-10 dimethicone, tocopheryl acetate, methicone, trimethylsiloxysilicate, sodium pca, sodium lactate, thermus thermophillus ferment, triethyl citrate, laureth-7, silica dimethyl silylate, polymethylsilsesquioxane, magnesium aluminum silicate, xanthan gum, dimethicone/peg-10/15 crosspolymer, sodium chloride, dextrin, triethoxycaprylylsilane, disteardimonium hectorite, caprylyl glycol, hexylene glycol, polyglutamic acid, zinc stearate, disodium edta, phenoxyethanol, potassium sorbate, sodium dehydroacetate [+/- mica, titanium dioxide (ci 77891), iron oxides (ci 77491), iron oxides (ci 77492), iron oxides (ci 77499)] <iln41311>

Other information

protect the product in this container from excessive heat and direct sun

DIST. BY: MAKE-UP ART COSMETICS
TORONTO, ONTARIO, CANADA M5V 1R7
LONDON W1K 3BQ / MXCT

PRINCIPAL DISPLAY PANEL - 30 ML Bottle Carton

M•A•C
STUDIO

STUDIO WATERWEIGHT
SPF 30 FOUNDATION
BROAD SPECTRUM SPF 30

30 ML/1.0 FL OZ e